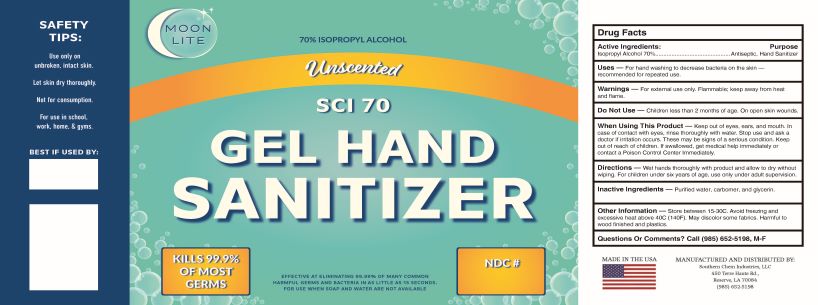 DRUG LABEL: SCI 70 Gel Hand Sanitizer
NDC: 55549-016 | Form: GEL
Manufacturer: Southern Chem Industries LLC
Category: otc | Type: HUMAN OTC DRUG LABEL
Date: 20201012

ACTIVE INGREDIENTS: ISOPROPYL ALCOHOL 70 mL/100 mL
INACTIVE INGREDIENTS: GLYCERIN 1.45 mL/100 mL; WATER; METHACRYLIC ACID - ETHYL ACRYLATE COPOLYMER (4500 MPA.S) 4 mL/100 mL

70 IPA Gel No HP

1. Isopropyl Alcohol (USP or Food Chemical Codex (FCC) grade) (70%, volume/volume (v/v)) in an aqueous solution denatured according to Alcohol and Tobacco Tax and Trade Bureau regulations in 27 CFR part 20.
2. Glycerol (1.45% v/v).
3. Hydrogen peroxide (0.125% v/v).
4. Sterile distilled water or boiled cold water.
5. Carbomer

Active Ingredient(s)

Isopropyl Alcohol 70% v/v. Purpose: Antiseptic

Purpose

Antiseptic, Hand Sanitizer

Use

For hand washing to decrease bacteria on the skin - Recommended for repeated use.

Warnings

For external use only. Flammable. Keep away from heat or flame

Do not use

- in children less than 2 months of age
- on open skin wounds

When using this product keep out of eyes, ears, and mouth. In case of contact with eyes, rinse eyes thoroughly with water.
Stop use and ask a doctor if irritation occurs. These may be signs of a serious condition.
Keep out of reach of children. If swallowed, get medical help immediately or contact a Poison Control Center immediately.

Stop use and ask a doctor if irritation or rash occurs. These may be signs of a serious condition.

Keep out of reach of children. If swallowed, get medical help or contact a Poison Control Center right away.

Directions

Wet hands thoroughly with product, and allow to dry without wiping. For children under six, use only under adult supervision.

Other information

- Store between 15-30C (59-86F)
- Avoid freezing and excessive heat above 40C (104F)
- May discolor some fabrics. Harmful to wood finishes and plastics

Inactive ingredients

glycerin, carbomer, and purified water USP